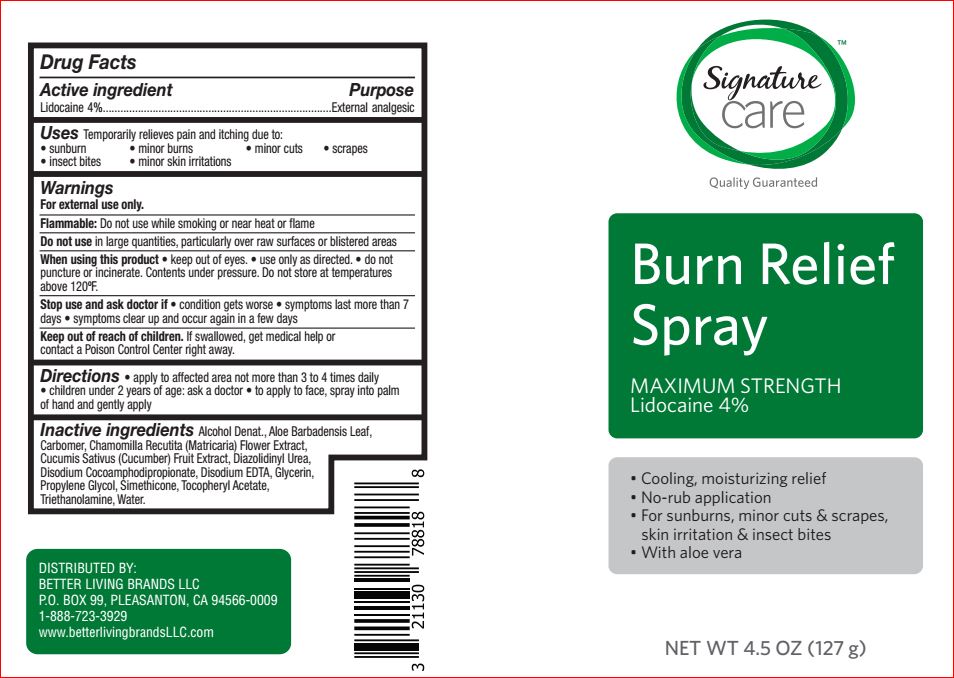 DRUG LABEL: Burn Relief
NDC: 21130-761 | Form: SPRAY
Manufacturer: Better Living
Category: otc | Type: HUMAN OTC DRUG LABEL
Date: 20180119

ACTIVE INGREDIENTS: Lidocaine 0.5 g/100 g
INACTIVE INGREDIENTS: ALOE VERA LEAF; Diazolidinyl Urea; Disodium Cocoamphodipropionate; EDETATE DISODIUM; Glycerin; Methylparaben; Propylene Glycol; Propylparaben; Alcohol; .ALPHA.-TOCOPHEROL ACETATE; TROLAMINE

Drug Facts

Active ingredient Purpose
Lidocaine 0.5%.............................................................Topical anesthetic

Uses
For temporary relief of pain associated with pain or itching due to : minor burns, sunburns, minor cuts, insect bites, skin irritation

Warnings
For external use only.

Flammable: Do not use while smoking or near heat or flame
When using this product • use only as directed • avoid contact with eyes

Do not puncture or incenerate. Contents under pressure. Do not store at temperature above 120F
Stop use and ask a doctor if • condition worsens • symptoms persist for more than 7 days or clear up and occur again within
a few days.

Keep out of reach of children. If swallowed, get medical help or contact a Poison Control Center immediately

Directions
Adults and children 2 years of age and older: Apply to affected area not more than 3 to 4 times daily. Children under 2 years of
age: consult a doctor.

Inactive ingredients

Aloe Barbadensis Leaf Extract
Carbomer
Diazolidinyl Urea
Disodium Cocoamphodipropionate
Disodium EDTA
Glycerin
Methylparaben
Propylene Glycol
Propylparaben
SD Alcohol 40
Simethicone
Tocopheryl Acetate
Triethanolamine